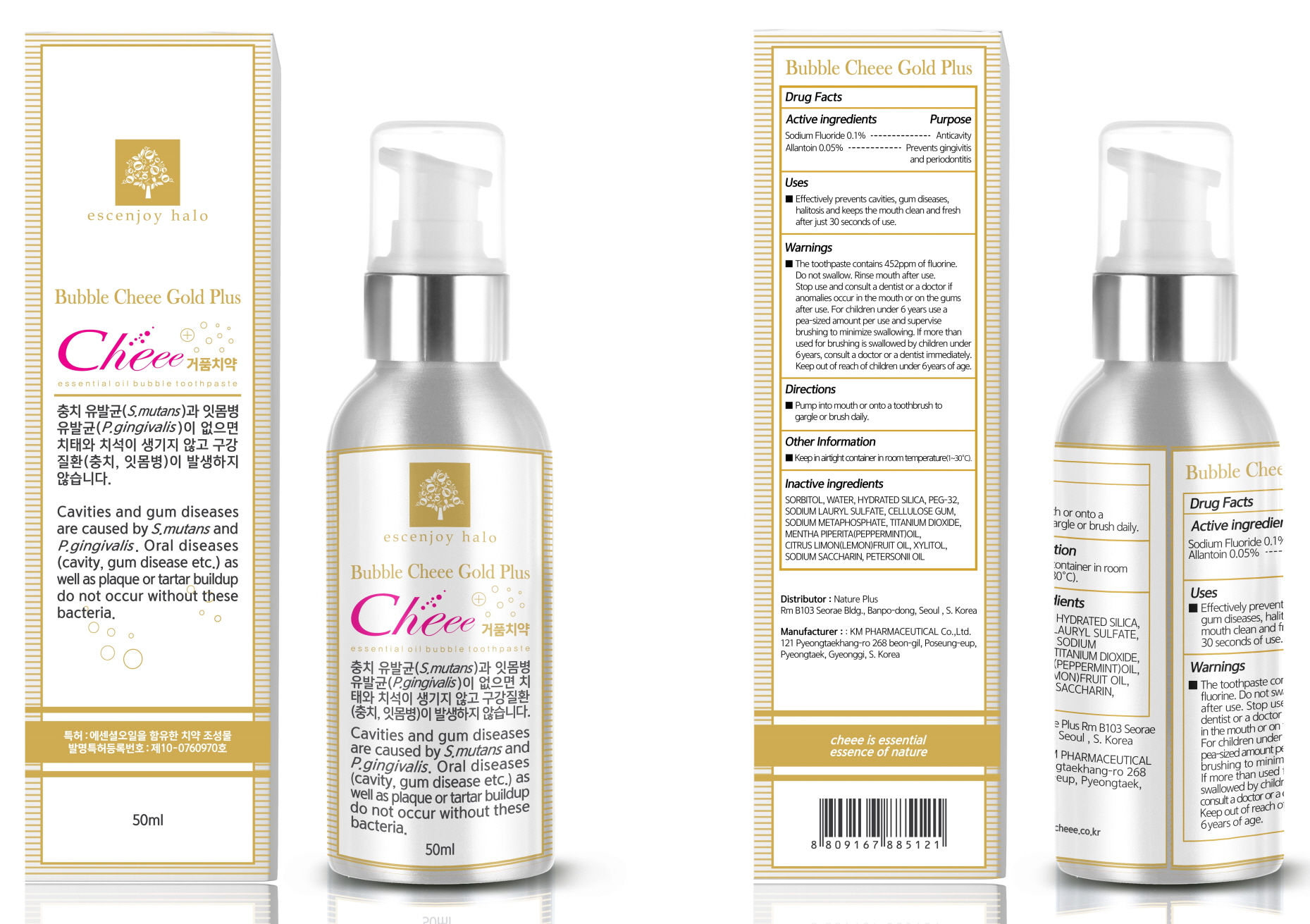 DRUG LABEL: Bubble Cheee Gold Plus Tooth
NDC: 79428-020 | Form: PASTE, DENTIFRICE
Manufacturer: Nature Plus
Category: otc | Type: HUMAN OTC DRUG LABEL
Date: 20200707

ACTIVE INGREDIENTS: Sodium Fluoride 0.05 g/50 mL; Allantoin 0.025 g/50 mL
INACTIVE INGREDIENTS: WATER; POLYOXYL 40 HYDROGENATED CASTOR OIL; SODIUM LAUROYL SARCOSINATE

ACTIVE INGREDIENTS

Sodium Fluoride 0.1%
Allantoin 0.05%

INACTIVE INGREDIENTS

Water, PEG-40 Hydrogenated castor oil, Sodium lauroyl sarcosinate, Xylitol, Mentha piperita(peppermint)oil, Citrus limon(lemon)Fruit oil, Methyl p-Hydroxy benzoate, Petersonii oil, Sodium saccharin

PURPOSE

Antiplaque
Prevents gingivitis and periodontitis

WARNINGS

The toothpaste contains 452ppm of fluorine. Do not swallow. Rinse mouth after use. Stop use and consult a dentist or a doctor if anomalies occur in the mouth or on the gums after use. For children under 6 years use a pea-sized amount per use and supervise brushing to minimize swallowing. If more than used for brushing is swallowed by children under 6 years, consult a doctor or a dentist immediately. Keep out of reach of children under 6 years of age.

Keep out of reach of children under 6 years of age.

Uses

Effectively prevents cavities, gum diseases, halitosis and keeps the mouth clean and fresh after just 30 seconds of use.

Directions

Pump into mouth or onto a toothbrush to gargle or brush daily.

Other Information

Keep in airtight container in room temperature(1~30°C).